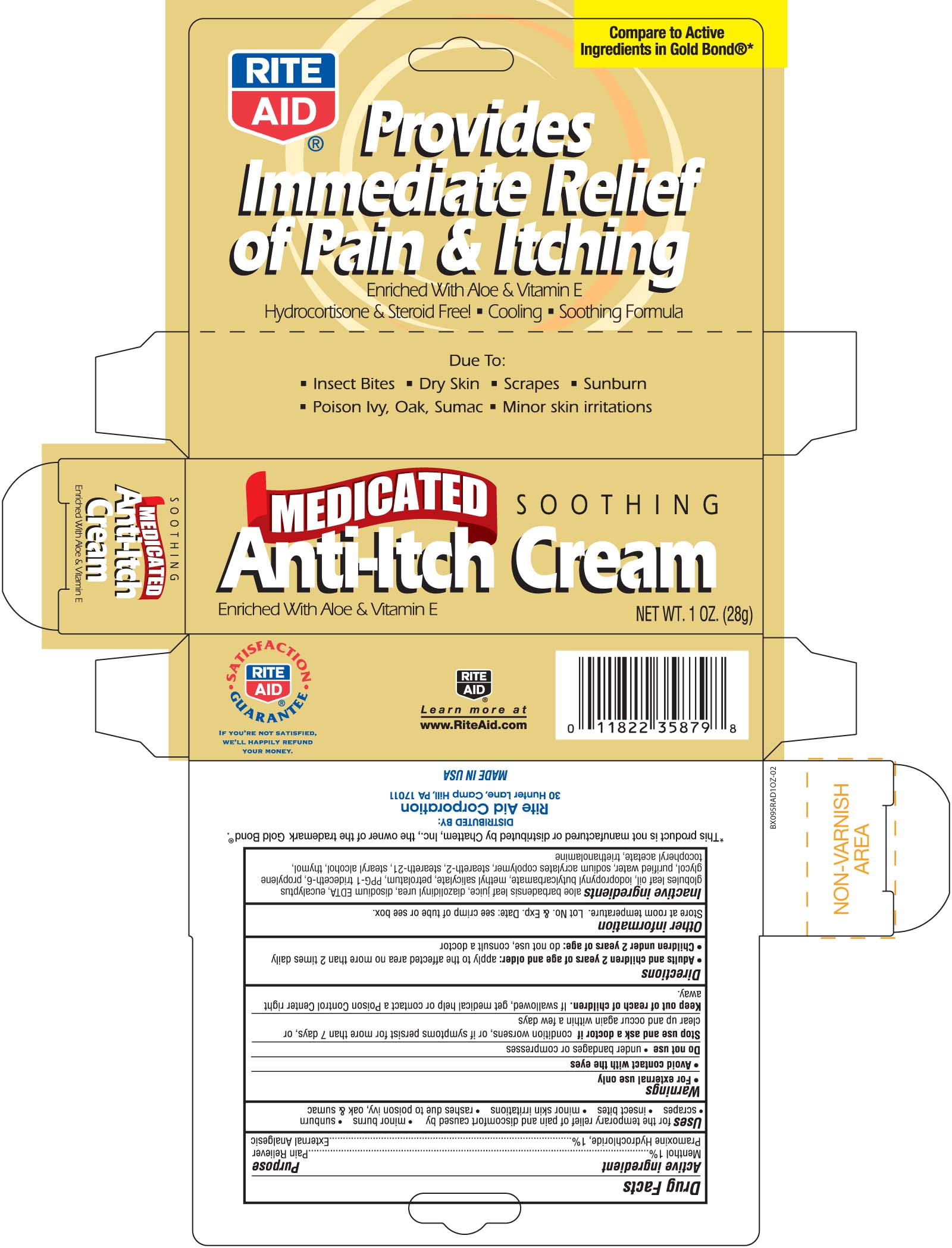 DRUG LABEL: Rite Aid Soothing Medicated Anit-Itch
NDC: 11822-0415 | Form: CREAM
Manufacturer: RITE AID CORPORATION
Category: otc | Type: HUMAN OTC DRUG LABEL
Date: 20100708

ACTIVE INGREDIENTS: PRAMOXINE HYDROCHLORIDE 10 mg/1 g; MENTHOL 10 mg/1 g
INACTIVE INGREDIENTS: WATER; STEARYL ALCOHOL; PETROLATUM; PROPYLENE GLYCOL; ALOE VERA LEAF; TRIDECETH-6; STEARETH-21; STEARETH-2; THYMOL; ALPHA-TOCOPHEROL; METHYL SALICYLATE; EDETATE DISODIUM; DIAZOLIDINYL UREA; TROLAMINE; IODOPROPYNYL BUTYLCARBAMATE; PROPYLENE GLYCOL; EUCALYPTUS OIL

DRUG FACTS

Active ingredient Purpose
Menthol 1%....................................................Pain Reliever
Pramoxine Hydrochloride 1%............................External Analgesic

Uses
For the temporary relief of pain and discomfort caused by
- minor burns - sunburn - scrapes - insect bites
- minor skin irritations - rashes due to poison ivy, oak and sumac

Keep out of reach of children. If swallowed, get medical help or contact a
Poison Control Center right away.

Uses
For the temporary relief of pain and discomfort caused by
- minor burns - sunburn - scrapes - insect bites
- minor skin irritations - rashes due to poison ivy, oak and sumac

Warnings
- For external use only
- Avoid contact with the eyes
Do Not use - under bandages or compresses
Stop use and ask a doctor if condition worsens, or if symptoms persist for more than 7 days or clear up and occur again within a few days.
Keep out of reach of children.If swallowed, get medical help or contact a Poison Control Center right away.

Directions
- Adults and children 2 years and older: apply to affected area not more than 2 times daily
- Children under 2 years of age: do not use, consult a doctor
Other information
Store at room temperature. Lot No. and Exp. Date: see crimp of tube or see box.

Inactive Ingredients
aloe barbadensis leaf juice, diazolidinyl urea, disodium EDTA, eucalyptus globules leaf oil, iodopropynyl butylcarbamate, methyl salicylate,
petrolatum, PPG-1 trideceth-6, propylene glycol, purified water, sodium acrylates copolymer, steareth-2 steareth-21, stearyl alcohol, thymol,
tocopheryl acetate, triethanolamine